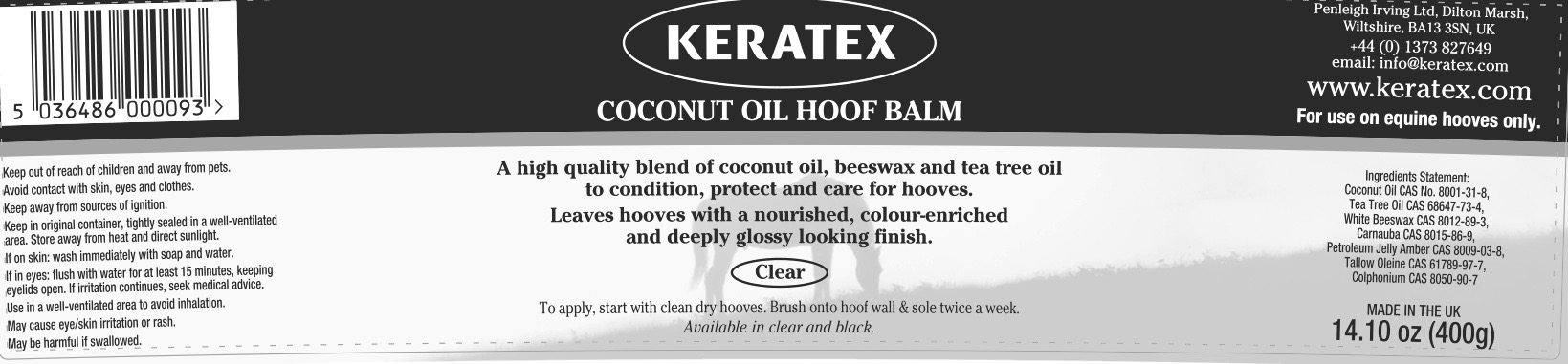 DRUG LABEL: Keratex
NDC: 27426-090 | Form: PASTE
Manufacturer: Penleigh Irving Ltd
Category: animal | Type: OTC ANIMAL DRUG LABEL
Date: 20181221

ACTIVE INGREDIENTS: COCONUT OIL 45.2 g/147 g; TEA TREE OIL 3.1 g/147 g

Keep out of reach of children and away from pets. Avoid contact with skin, eyes and clothes. Keep away from sources of ignition. Keep in original container, tightly sealed in a well-ventilated area. Store away from heat and direct sunlight. If on skin: wash immediately with soap and water. If in eyes : flush with water for at least 15 minutes, keeping eyelids open. If irritation continues, seek medical advice. Use in a well-ventilated area to avoid inhalation. May cause eye/skin irritation or rash. May be harmful if swallowed.

PACKAGE LABEL

Keratex Coconut Oil Hoof Balm. Clear.

A high quality blend of coconut oil, beeswax and tea tree oil to condition, protect and care for hooves.

Leaves hooves with a nourished, colour-enriched and deeply glossy looking finish.

To apply, start with clean dry hooves. Brush onto hoof wall and sole twice a week.

Available in clear and black.

Ingredients Statement: Coconut Oil CAS No. 8001-31-8, Tea Tree Oil CAS 68647-73-4, White Beeswax CAS 8012-89-3, Carnauba CAS 8015-86-9, Petroleum Jelly Amber CAS 8009-03-8, Tallow-Oleine CAS 61789-97-7, Colophonium CAS 8050-90-7

MADE IN THE UK

14.10 oz (400g)

Penleigh Irving Ltd, Dilton Marsh, Wiltshire, BA13 3SN, UK

+44 (0) 1373 827649 email: info@keratex.com www.keratex.com

For use on equine hooves only.